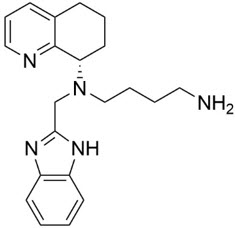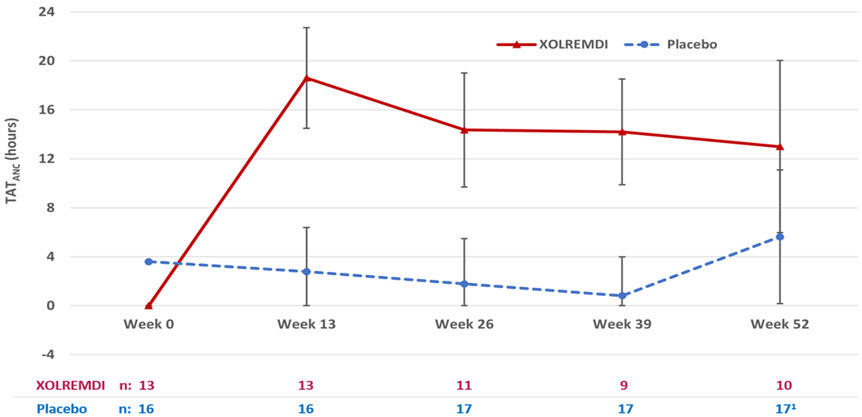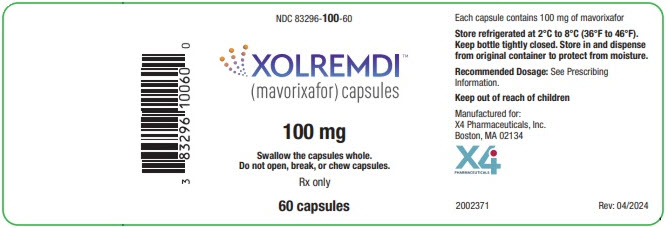 DRUG LABEL: XOLREMDI
NDC: 83296-100 | Form: CAPSULE, GELATIN COATED
Manufacturer: X4 Pharmaceuticals, Inc.
Category: prescription | Type: HUMAN PRESCRIPTION DRUG LABEL
Date: 20241112

ACTIVE INGREDIENTS: MAVORIXAFOR 100 mg/1 1
INACTIVE INGREDIENTS: MICROCRYSTALLINE CELLULOSE; DIBASIC CALCIUM PHOSPHATE DIHYDRATE; CROSCARMELLOSE SODIUM; SODIUM LAURYL SULFATE; SILICON DIOXIDE; SODIUM STEARYL FUMARATE

HIGHLIGHTS OF PRESCRIBING INFORMATION

These highlights do not include all the information needed to use XOLREMDI™ safely and effectively. See full prescribing information for XOLREMDI®.
XOLREMDI®(mavorixafor) capsules, for oral use
Initial U.S. Approval: 2024

1 INDICATIONS AND USAGE

XOLREMDI is a CXC chemokine receptor 4 antagonist indicated in patients 12 years of age and older with WHIM syndrome (warts, hypogammaglobulinemia, infections and myelokathexis) to increase the number of circulating mature neutrophils and lymphocytes. (1)

2 DOSAGE AND ADMINISTRATION

- Recommended dosage:
  - Weight more than 50 kg: 400 mg orally once daily. (2)
  - Weight less than or equal to 50 kg: 300 mg orally once daily. (2)
- Administer XOLREMDI on an empty stomach after an overnight fast, and at least 30 minutes before food. (2)

3 DOSAGE FORMS AND STRENGTHS

Capsules: 100 mg mavorixafor. (3)

4 CONTRAINDICATIONS

Use with drugs highly dependent on CYP2D6 for clearance. (4, 7.2)

5 WARNINGS AND PRECAUTIONS

- Embryo-fetal toxicity: Expected to cause fetal harm. Advise women of reproductive potential to use effective contraception. (5.1, 8.1, 8.3)
- QTc Interval Prolongation: : Correct any modifiable risk factors, assess QTc at baseline and monitor QTc during treatment as clinically indicated. XOLREMDI dose reduction or discontinuation may be required due to drug-drug interactions. (5.2)

6 ADVERSE REACTIONS

The most common adverse reactions (›10% and at a frequency higher than placebo) were: thrombocytopenia, pityriasis, rash, rhinitis, epistaxis, vomiting, and dizziness. (6.1)

To report SUSPECTED ADVERSE REACTIONS, contact X4 Pharmaceuticals, Inc. at 1-866-MED-X4MI (1-866-633-9464) or FDA at 1-800-FDA-1088 or www.fda.gov/medwatch.

7 DRUG INTERACTIONS

- Strong CYP3A4 inhibitors: Reduce XOLREMDI daily dosage. (2.2, 7.1)
- P-gp inhibitors or moderate CYP3A4 inhibitors: Monitor more frequently for XOLREMDI adverse reactions and reduce XOLREMDI daily dosage if necessary. (7.1)
- Strong CYP3A4 Inducers: Avoid concomitant use. (7.1)
- CYP3A4 or P-gp substrates: Monitor more frequently for substrate adverse reactions unless otherwise recommended. (7.2)

8 USE IN SPECIFIC POPULATIONS

- Lactation: Advise females that breastfeeding is not recommended. (8.2)
- Renal Impairment: Not recommended for use in patients with severe renal impairment or end stage renal disease. (8.6)
- Hepatic Impairment: Not recommended for use in patients with moderate to severe hepatic impairment. (8.7)

FULL PRESCRIBING INFORMATION

1 INDICATIONS AND USAGE

XOLREMDI is indicated in patients 12 years of age and older with WHIM syndrome (warts, hypogammaglobulinemia, infections and myelokathexis) to increase the number of circulating mature neutrophils and lympocytes.

2 DOSAGE AND ADMINISTRATION

2.1 Recommended Dosage

The recommended dosage of XOLREMDI is:

- Weight more than 50 kg: 400 mg orally once daily on an empty stomach after an overnight fast, and at least 30 minutes before food.
- Weight less than or equal to 50 kg: 300 mg orally once daily on an empty stomach after an overnight fast, and at least 30 minutes before food.

Swallow the capsules whole. Do not open, break, or chew capsules.

If a dose of XOLREMDI is missed, the next dose should be taken as scheduled. Do not take more than 1 XOLREMDI dose each day.

2.2 Dosage Modifications for Strong CYP3A4 inhibitors

Reduce daily dosage of XOLREMDI to 200 mg when used concomitantly with strong CYP3A4 inhibitors [see Drug Interactions (7.1)] .

3 DOSAGE FORMS AND STRENGTHS

Capsules: 100 mg, opaque hard gelatin capsules with white body and light blue cap. The white capsule body is imprinted with "100 mg" in black ink, and the light blue capsule cap is imprinted with "MX4" in black ink.

4 CONTRAINDICATIONS

Use of XOLREMDI is contraindicated with drugs that are highly dependent on CYP2D6 for clearance [see Drug Interactions (7.2)] .

5 WARNINGS AND PRECAUTIONS

5.1 Embryo-Fetal Toxicity

Based on its mechanism of action, XOLREMDI is expected to cause fetal harm when administered to a pregnant woman [see Clinical Pharmacology (12.2)] . Animal models link reductions in CXCR4/SDF-1 signaling to adverse outcomes in mammalian embryo-fetal development and to abnormal placental development.

Verify the pregnancy status of female patients of reproductive potential prior to starting XOLREMDI. Advise females of reproductive potential to use an effective method of contraception during treatment with XOLREMDI and for 3 weeks after the final dose [see Use in Specific Populations (8.1, 8.3)] .

5.2 QTc Interval Prolongation

XOLREMDI causes concentration-dependent QTc interval prolongation. QTc interval prolongation may occur when XOLREMDI is taken with concomitant medications that increase XOLREMDI exposure and/or drug products with a known potential to prolong QTc. Correct any modifiable risk factors for QTc prolongation (e.g., hypokalemia), assess QTc at baseline and monitor QTc during treatment as clinically indicated in patients with risk factors for QTc prolongation such as those receiving concomitant medications that increase XOLREMDI exposure and drug products with a known potential to prolong QTc. A dose reduction in XOLREMDI or discontinuation of XOLREMDI may be required [see Drug Interactions (7.1, 7.3) and Clinical Pharmacology (12.2)].

6 ADVERSE REACTIONS

The following clinically significant adverse reactions are described elsewhere in the labeling:

- QTc Interval Prolongation [see Warnings and Precautions (5.2)]

6.1 Clinical Trials Experience

Because clinical trials are conducted under widely varying conditions, adverse reaction rates observed in the clinical trials of a drug cannot be directly compared to rates in the clinical trials of another drug and may not reflect the rates observed in practice.

The safety of XOLREMDI was evaluated in Study 1, a randomized placebo-controlled trial of 31 adult and pediatric patients 12 years and older with WHIM syndrome [see Clinical Studies (14)] . Patients received XOLREMDI 400 mg or 200 mg, based on age and body weight (N=14) or placebo (N=17). One patient received the 200 mg dose, and 13 patients received the 400 mg dose. Note that the 200 mg XOLREMDI daily dose is only recommended for use in patients receiving strong CYP3A4 inhibitors [see Dosage and Administration (2.1, 2.2)] . For all other patients, the recommended dosage is either 400 mg daily (if weighing more than 50 kg) or 300 mg daily (if weighing up to 50 kg), unless dose reductions are needed due to concomitant use with moderate CYP3A4 inhibitors or P-gp inhibitors [see Drug Interactions (7.1)] .

The data below are based on the 52-week, placebo-controlled portion of the study. Twelve patients received XOLREMDI for at least 6 months, and 10 patients received XOLREMDI for at least 1 year.

Table 1 summarizes the most common adverse reactions (>10%) in Study 1, which were thrombocytopenia, pityriasis, rash, rhinitis, epistaxis, vomiting, and dizziness.

Table 1: Adverse Reactions in ≥10% Patients with WHIM Syndrome Receiving XOLREMDI and More Frequently Reported than Placebo During Study 1
 | Number (N) and Percent (%) of Patients
Adverse Reaction | XOLREMDI (N=14) | Placebo (N=17)
Thrombocytopenia | 3 (21%) | 0
Pityriasis | 2 (14%) | 0
Rash | 2 (14%) | 0
Rhinitis | 2 (14%) | 0
Epistaxis | 2 (14%) | 1 (6%)
Vomiting | 2 (14%) | 1 (6%)
Dizziness | 2 (14%) | 1 (6%)

Serious adverse reactions of thrombocytopenia occurred in 3 of the 14 patients who received XOLREMDI, 2 of which occurred in the setting of infection or febrile neutropenia.

7 DRUG INTERACTIONS

7.1 Effect of Other Drugs on XOLREMDI

Strong or Moderate CYP3A4 Inhibitors

Reduce XOLREMDI daily dosage to 200 mg when used concomitantly with a strong CYP3A4 inhibitor [see Dosage and Administration (2.2)] .

Monitor more frequently for XOLREMDI adverse reactions that may be associated with an increase in mavorixafor exposure when used concomitantly with moderate CYP3A4 inhibitor and reduce the XOLREMDI daily dosage by steps of 100 mg, if necessary, but not to a dose less than 200 mg.

Mavorixafor is a CYP3A4 substrate. Concomitant use with a strong CYP3A4 inhibitor increases mavorixafor maximal concentrations (Cmax) and area under the concentration-time curve (AUC) [see Clinical Pharmacology (12.3)] , which may increase the risk of XOLREMDI adverse reactions.

Strong CYP3A4 Inducers

Avoid concomitant use with a strong CYP3A4 inducer.

Mavorixafor is a CYP3A4 substrate. Concomitant use with a strong CYP3A4 inducer is predicted to decrease mavorixafor Cmaxand AUC based upon a mechanistic understanding of its elimination [see Clinical Pharmacology (12.3)] , which may reduce XOLREMDI's effectiveness.

P-gp Inhibitors

Monitor more frequently for XOLREMDI adverse reactions that may be associated with an increase in mavorixafor exposure when used concomitantly with P-gp inhibitors and reduce the XOLREMDI daily dosage by steps of 100 mg, if necessary, but not to a dose less than 200 mg.

Mavorixafor is a P-gp substrate. Concomitant use with a P-gp inhibitors increases mavorixafor Cmaxand AUC [see Clinical Pharmacology (12.3)] , which may increase the risk of XOLREMDI adverse reactions.

7.2 Effect of XOLREMDI on Other Drugs

CYP2D6 Substrates

The use of XOLREMDI with drugs that are another drug highly dependent on CYP2D6 for clearance is contraindicated [see Contraindications (4)] .

Mavorixafor is a CYP2D6 inhibitor. Mavorixafor increases exposure of CYP2D6 substrates [see Clinical Pharmacology (12.3)] , which may increase the risk of adverse reactions related to these substrates.

CYP3A4 Substrates

Monitor for CYP3A4 substrate related adverse reactions more frequently, unless otherwise recommended in the substrate's Prescribing Information, when XOLREMDI is used concomitantly with CYP3A4 substrates where minimal substrate concentration changes may lead to serious adverse reactions.

Mavorixafor is an inhibitor of CYP3A4. Mavorixafor may increase the Cmaxand AUC of CYP3A4 substrates [see Clinical Pharmacology (12.3)] , which may increase the risk of adverse reactions from the CYP3A4 substrate.

P-gp Substrates

Monitor for P-gp substrate related adverse reactions more frequently, unless otherwise recommended in the substrate's Prescribing Information, when XOLREMDI is used concomitantly with P-gp substrates where minimal substrate concentration changes may lead to serious adverse reactions.

Digoxin: Measure serum digoxin concentrations before initiating concomitant use with XOLREMDI, and continue monitoring serum digoxin concentrations as recommended in the Prescribing Information for digoxin [see Clinical Pharmacology (12.3)] .

Mavorixafor is an inhibitor of P-gp. Mavorixafor may increase the Cmaxand AUC of P-gp substrates [see Clinical Pharmacology (12.3)] , which may increase the risk of adverse reactions from the P-gp substrate.

Metformin: Monitor for glycemic control and adjust the dose of metformin as necessary. Mavorixafor may decrease the mean Cmaxand AUC of metformin, which may reduce metformin's effectiveness. The mechanism of this interaction is unknown.

7.3 Drugs that Prolong the QTc Interval

Obtain an electrocardiogram when initiating, during concomitant use, and as clinically indicated in patients receiving concomitant medications with a known potential to prolong the QTc interval [see Warnings and Precautions (5.2)] .

XOLREMDI causes QTc interval prolongation [see Clinical Pharmacology (12.2)] . Concomitant use of XOLREMDI with other products that prolong QTc interval may result in a greater increase in QTc interval and adverse reactions associated with QTc interval prolongation, including torsade de pointes, other serious arrythmias, and sudden death [see Warnings and Precautions (5.2)] .

8 USE IN SPECIFIC POPULATIONS

8.1 Pregnancy

Risk Summary

Based on its mechanism of action, XOLREMDI is expected to cause fetal harm when administered to a pregnant woman [see Clinical Pharmacology (12.1)] . There are no available data on XOLREMDI use in pregnant women informing the risk of embryo-fetal developmental toxicities. Animal models link reductions in CXCR4/SDF-1 signaling to adverse outcomes in mammalian embryo-fetal development (see Data) . No definitive animal studies have been conducted to evaluate the effect of mavorixafor on reproduction and fetal development.

Advise pregnant women of the potential risk to the fetus and to use effective contraception [see Warnings and Precautions (5.1)and Use in Specific Populations (8.3)] .

The estimated background risk of major birth defects and miscarriages for the indicated population is unknown. All pregnancies have a background risk of birth defect, loss, or other adverse outcomes. In the U.S. general population, the estimated background risk of major birth defects and miscarriage in clinically recognized pregnancies is 2% to 4% and 15% to 20%, respectively.

Data

Animal Data

Animal reproduction studies have not been conducted with mavorixafor to evaluate effects on reproduction and embryo-fetal development. CXCR4/SDF-1 signaling plays an important role in mammalian embryo-fetal and placental development. In mice, CXCR4-/- knockout is embryo lethal and causes multiple developmental toxicities, most notably in the hematopoietic, cardiovascular and nervous systems. CXCR4/SDF-1 levels have a key role in stimulating trophoblast proliferation and differentiation necessary for appropriate placental growth and function in humans [see Warnings and Precautions (5.1)].

8.2 Lactation

Risk Summary

There are no data on the presence of mavorixafor in human or animal milk, the effects on the breastfed child, or the effects on milk production. Because of the potential for serious adverse reactions in the breastfed child, advise females that breastfeeding is not recommended during treatment with XOLREMDI and for 3 weeks after the final dose.

8.3 Females and Males of Reproductive Potential

XOLREMDI is expected to cause fetal harm when administered to pregnant women [see Warnings and Precautions (5.1)and Use in Specific Populations (8.1)] .

Pregnancy Testing

Verify the pregnancy status in females of reproductive potential prior to initiating XOLREMDI [see Use in Specific Populations (8.1)] .

Contraception

Advise females of reproductive potential to use an effective form of contraception during treatment with XOLREMDI and for 3 weeks after the final dose [see Use in Specific Populations (8.1)].

8.4 Pediatric Use

The safety and effectiveness of XOLREMDI in WHIM syndrome for increasing the number of circulating mature neutrophils and lymphocytes have been established in pediatric patients aged 12 years and older. Use of XOLREMDI for this indication is supported by evidence from an adequate and well-controlled study in adults and pediatric patients aged 12 years and older [see Clinical Pharmacology (12.3)and Clinical Studies (14)] .

The safety and effectiveness of XOLREMDI have not been established in pediatric patients younger than 12 years of age.

8.5 Geriatric Use

In clinical studies of XOLREMDI in patients with WHIM syndrome, 2 (5%) patients were aged 65 years and older, and no patients were aged 75 years and older. Clinical studies did not include sufficient numbers of patients aged 65 and older to determine whether they respond differently from younger patients.

8.6 Renal Impairment

XOLREMDI is not recommended in patients with severe renal impairment (creatinine clearance [CLcr] 15 to less than 30 mL/min) or end-stage renal disease (CLcr less than 15 mL/min). No dosage adjustment is recommended in patients with mild to moderate renal impairment (CLcr 30 to less than 90 mL/min).

No clinically significant differences in the pharmacokinetics of mavorixafor were observed in mild to moderate renal impairment (CLcr 30 to less than 90 mL/min). The pharmacokinetics of mavorixafor have not been studied in subjects with severe renal impairment or end-stage renal disease [see Clinical Pharmacology (12.3)] .

8.7 Hepatic Impairment

XOLREMDI is not recommended for use in patients with moderate to severe hepatic impairment. No dosage adjustment is recommended in patients with mild hepatic impairment.

The pharmacokinetics of mavorixafor have not been studied in subjects with moderate to severe hepatic impairment [ see Clinical Pharmacology (12.3)].

11 DESCRIPTION

Mavorixafor is an orally bioavailable CXC Chemokine Receptor 4 (CXCR4) antagonist [see Clinical Pharmacology (12.1)] .

The chemical name of the active ingredient, mavorixafor, is N^1-(1 H-benzimidazol-2-ylmethyl)- N^1-[(8 S)-5,6,7,8-tetrahydroquinolin-8-yl]butane-1,4-diamine. It has a molecular formula of C21H27N5and a molecular weight of 349.48 g/mol. Mavorixafor is of the Sconfiguration and its structural formula is provided in Figure 1.

Figure 1: Structural Formula

Mavorixafor is optically active and is a white to pale yellow to light brown solid. Mavorixafor is hygroscopic above relative humidities of 70%.

Mavorixafor is freely soluble in methanol, 95% ethanol and n-octanol, soluble in toluene, sparingly soluble in DMSO and acetonitrile, and very slightly soluble in HPLC grade water according to the USP solubility criteria.

Mavorixafor is soluble in pH 1.2 to 5.5 aqueous buffers and in pH 6.0 aqueous buffer, sparingly soluble in pH 6.8 aqueous buffer and slightly soluble in pH 7.5 aqueous buffer, according to the USP solubility criteria.

XOLREMDI is a hard gelatin capsule for oral administration. Each capsule contains 100 mg of mavorixafor with the following inactive ingredients: colloidal silicon dioxide, croscarmellose sodium, dibasic calcium phosphate dihydrate, microcrystalline cellulose, sodium lauryl sulfate, and sodium stearyl fumarate. The hard gelatin capsule contains FD&C Blue #2, gelatin, and titanium dioxide. The Black Ink contains ammonium hydroxide 28%, ferrosoferric oxide/black iron oxide (E172), isopropyl alcohol, n-butyl alcohol, propylene glycol, and shellac glaze in ethanol.

12 CLINICAL PHARMACOLOGY

12.1 Mechanism of Action

Mavorixafor is an orally bioavailable CXCR4 antagonist that blocks the binding of the CXCR4 ligand, stromal-derived factor-1α (SDF-1α)/CXC Chemokine Ligand 12 (CXCL12). SDF-1/CXCR4 plays a role in trafficking and homing of leukocytes to and from the bone marrow compartment. Gain of function mutations in the CXCR4 receptor gene that occur in patients with WHIM syndrome lead to increased responsiveness to CXCL12 and retention of leukocytes in the bone marrow. Mavorixafor inhibits the response to CXCL12 in both wild‑type and for mutated CXCR4 variants associated with WHIM syndrome. Treatment with mavorixafor results in increased mobilization of leukocytes and lymphocytes from the bone marrow into peripheral circulation.

12.2 Pharmacodynamics

Absolute Neutrophil Count (ANC) and Absolute Lymphocyte Count (ALC)

ANC and ALC peaked at 4 hours after XOLREMDI dosing and returned towards baseline within 24 h after dosing. Over mavorixafor doses of 50 mg (0.125 times the maximum recommended dosage) to 400 mg once daily, higher mavorixafor exposure at steady state was associated with longer mean time (hours) above ANC threshold (TATANC) of 500 cells/µL and longer mean time (hours) above ALC threshold (TATALC) of 1,000 cells/µL over a 24-hour period.

Cardiac Electrophysiology

In a thorough QT (TQT) study, the maximum mean increase in the QTc interval was 15.6 ms (upper bound of the 90% confidence interval = 19.8 ms) after administration of XOLREMDI 800 mg (2 times the maximum recommended dose) in healthy volunteers [ see Warnings and Precautions (5.2)]. In concentration-QT analysis, increase in QTc interval was concentration-dependent.

12.3 Pharmacokinetics

Mavorixafor pharmacokinetic parameters are presented as geometric mean (CV%) in adults with WHIM syndrome unless otherwise specified. Mavorixafor steady state Cmaxis 3304 (58.6%) ng/mL and the AUC from 0 to 24 hours (AUC0-24h) is 13970 (58.4%) ng*h/mL following 400 mg once daily.

Mavorixafor demonstrates nonlinear pharmacokinetics with greater than dose-proportional increases in Cmaxand AUC0-24over a dose range of 50 mg (0.125 times the recommended dosage) to 400 mg. Mavorixafor steady state is reached after approximately 9 to 12 days at the highest approved recommended dosage in healthy subjects.

Absorption

Mavorixafor median (range) time to Cmax(Tmax) is 2.8 hours (1.9 to 4 hours) at the highest approved recommended dosage.

Effect of Food

High Fat Meal:Mavorixafor Cmaxdecreased by 66% and AUC decreased by 55% following single-dose administration of XOLREMDI 400 mg with a high‑fat meal (1000 calories, 50% fat) to healthy subjects.

Low Fat Meal:Mavorixafor Cmaxdecreased by 55% and AUC decreased by 51% following single-dose administration of XOLREMDI 400 mg with a low-fat meal (500 calories, 25% fat) to healthy subjects. In addition, a 14% higher mavorixafor Cmaxand 18% lower AUC was observed following single-dose administration of XOLREMDI 400 mg with a low-fat meal to healthy subjects after an overnight fast compared to fasting for an additional 4 hours after the XOLREMDI dose.

Distribution

Mavorixafor volume of distribution is 768 L. Mavorixafor is >93% bound to human plasma proteins in vitro.

Elimination

Mavorixafor's terminal half-life is 82 h (34%) with an apparent clearance of 62 L/h (40%) following single-dose administration of XOLREMDI 400 mg in health subjects. Mavorixafor exhibits at least partial nonlinear apparent clearance; however, this is not clinically significant at the approved recommended dosage.

Metabolism

CYP3A4 and, to a lesser extent, CYP2D6 are primarily responsible for mavorixafor metabolism.

Excretion

After a single oral dose of radiolabeled mavorixafor, 74.2% of the administered dose was recovered out of which 61.0% of administered radioactivity was recovered in feces and 13.2% (3% unchanged) was recovered in the urine over the 240-hour collection period in healthy subjects.

Specific Populations

No clinically significant differences in the pharmacokinetics of mavorixafor were observed based on age (12 to 58 years), sex, or mild to moderate renal impairment (CLcr 30 to <90 mL/min as estimated by the Cockcroft-Gault formula). The effects of severe renal impairment (CLcr 15 to <30 mL/min), end-stage renal disease (CLcr <15 mL/min), and moderate to severe hepatic impairment on the pharmacokinetics of mavorixafor are unknown.

Lower body weight was associated with lower mavorixafor clearance. Mavorixafor exposures in patients with WHIM syndrome are comparable between those weighing 50 kg or less who receive 300 mg once daily and those weighing greater than 50 kg who receive 400 mg once daily. Following 400 mg once daily, median Cmaxand AUC is 22% and 30% lower, respectively, in patients with higher body weight (85 kg and above) compared to patients with average body weight (50 to less than 85 kg). The difference in exposure between patients with average body weight and patients with higher body weight is not expected to have a clinically significant impact on patient outcomes.

Pediatric Patients

No clinically significant differences in the pharmacokinetics of mavorixafor were identified in pediatric patients aged 12 to <17 years with WHIM syndrome compared to adult patients after accounting for differences in body weight.

Drug Interaction Studies

Clinical Studies

Strong CYP3A4 Inhibitors:The systemic exposures of mavorixafor following concomitant administration of a single dose of XOLREMDI 200 mg (0.5 times the recommended dosage for adult and adolescent patients 12 years and older weighing over 50 kg) with 200 mg itraconazole (strong CYP3A4 inhibitor and P-gp inhibitor) dosed to steady state was similar to the mavorixafor systemic exposure from a single dose of XOLREMDI 400 mg administered alone in healthy subjects. These results suggest an approximate increase in mavorixafor exposure by 2-fold due to itraconazole.

CYP2D6 Substrates:Dextromethorphan (CYP2D6 substrate) Cmaxincreased by 6-fold (CI90%: 5.1 to 8.3) and AUC by 9-fold (CI90%: 6.5 to 12.3) following concomitant use with XOLREMDI 400 mg in healthy subjects.

CYP3A4 Substrates:Midazolam (CYP3A4 substrate) Cmaxincreased by 1.1-fold (CI90%: 1.0 to 1.3) and AUC by 1.7-fold (CI90%: 1.4 to 2.1) following concomitant use with XOLREMDI 400 mg in healthy subjects.

P-gp Substrates:

Digoxin:Digoxin Cmaxincreased by 1.5-fold (CI90%: 1.3 to 1.8) and AUC increased by 1.6-fold (CI90%: 1.4 to 1.9) following concomitant use of a single oral dose of a transporter cocktail containing 0.25 mg of digoxin with XOLREMDI dosed to steady state (400 mg/day) in healthy subjects.

Metformin:Metformin Cmaxdecreased by 35% (CI90%: 17 to 49%) and AUC decreased by 35% (CI90%: 20 to 47%) following concomitant use of a single oral dose of a transporter cocktail containing 10 mg of metformin with XOLREMDI dosed to steady state (400 mg/day) in healthy subjects.

Other Drugs: No clinically significant differences in the pharmacokinetics of caffeine (CYP1A2 substrate), losartan (CYP2C9 substrate), omeprazole (CYP2C19 substrate), furosemide (OAT1 and OAT3 substrate) and oral contraceptives were observed following concomitant use with mavorixafor.

In Vitro Studies

CYP450 Enzymes:Mavorixafor is a substrate of CYP3A4, CYP2D6, CYP3A5, and CYP2C19, but is not a substrate of CYP1A2, CYP2A6, CYP2B6, CYP2C8, CYP2C19, CYP2E1, and CYP4A11. Mavorixafor is an inhibitor of CYP3A4 (time dependent), CYP3A5, CYP2D6, CYP2B6, CYP1A2, CYP2C8, CYP2C9, and CYP2C19. Mavorixafor is an inducer of CYP1A2, but not an inducer of CYP2B6, CYP2C8, CYP2C9 and CYP3A4.

Transporter Systems:Mavorixafor is a substrate of P-gp, but not a substrate of OATP1B1, OATP1B3, OAT1, OAT3, OCT2, MATE1 or MATE2-K. Mavorixafor is an inhibitor of P-gp, OCT2, and MATE1, but is not an inhibitor of BCRP, OATP1B1, OATP1B3, OAT1, OAT3, and MATE2-K.

13 NONCLINICAL TOXICOLOGY

13.1 Carcinogenesis, Mutagenesis, Impairment of Fertility

Carcinogenicity studies with mavorixafor have not been conducted.

Mavorixafor was not genotoxic in an in vitrobacterial reverse mutation assay (Ames test), in an in vitrohuman lymphocyte culture chromosome aberration assay, or an in vivorat bone marrow micronucleus assay.

Fertility studies have not been conducted with mavorixafor. Significant tubular degeneration/atrophy was observed in the testes of dogs at clinical exposure.

14 CLINICAL STUDIES

The efficacy of XOLREMDI in patients aged 12 and older with WHIM syndrome was demonstrated in the 52-week, randomized, double-blind, placebo-controlled portion of Study 1 [ NCT03995108]. Enrolled patients had a genotype-confirmed variant of CXCR4 consistent with WHIM syndrome, and a confirmed absolute neutrophil count (ANC) ≤400 cells/µL. Patients were permitted to continue (but not initiate) immunoglobulin therapy at the same dose. Use of other CXCR4 antagonists was not permitted. Baseline patient demographics are shown in Table 2.

Table 2: Baseline Demographic and Disease Characteristics in Patients with WHIM Syndrome (Study 1)
Demographics and Disease Characteristics | XOLREMDI (N = 14) | Placebo (N = 17)
Demographics
Age(years) Mean (SD) | 22.1 (12.20) | 30.9 (21.25)
Age group, n (%)
12 to <18 years | 7 (50) | 8 (47.1)
≥18 years | 7 (50) | 9 (52.9)
Sex, n (%)
Male | 5 (35.7) | 8 (47.1)
Female | 9 (64.3) | 9 (52.9)
Race, n (%)
White | 13 (93) | 16 (94)
Asian | 0 | 1 (6)
Other | 1 (7) | 0
Ethnicity, n (%)
Not Hispanic or Latino | 13 (93) | 17 (100)
Hispanic or Latino | 1 (7) | 0
Disease Characteristics
Baseline Ig use, n (%)
Yes | 6 (42.9) | 8 (47.1)
Baseline mean absolute neutrophil count (ANC)(cells/µL) Mean (SD) | 155 (93.8) | 281 (232.7)
Baseline mean absolute lymphocyte count (ALC)(cells/µL) Mean (SD) | 501 (204.8) | 563 (199.1)
Abbreviations: SD = standard deviation; Ig = immunoglobulin.
Note: Percentages are calculated based on the number of patients within each characteristic as denominator.

Thirty-one patients were randomized 1:1 to receive either placebo (N=17) or XOLREMDI (N=14) once daily for 52 weeks. The efficacy of XOLREMDI in the treatment of patients with WHIM syndrome was based on improvement in absolute neutrophil counts (ANC), improvement in absolute lymphocyte counts (ALC), and a reduction in infections.

For ANC, the mean time (hours) above ANC threshold (TATANC) of 500 cells/µL over a 24-hour period was assessed 4 times throughout the study (every 3 months for 12 months). The results over the 52-week period showed that TATANCwas statistically significantly greater in patients treated with XOLREMDI (LS mean [SE] 15.0 [1.89] hours) compared with placebo (2.8 [1.52] hours) (p value <0.0001) (see Table 3and Figure 2).

Table 3 Mean Time (hours) Above ANC Threshold (TATANC) in Study 1
 |  | XOLREMDI (N = 14) | Placebo (N = 17)
Abbreviations: ANC = absolute neutrophil count; CI = confidence interval; LS = least squares; MMRM = mixed-model repeated measures; SD = standard deviation; SE = standard error; TAT = time above threshold of 500 cells/µL.
TATANC(hours)
Baseline | Mean (SD) | 0.0 (0.0) | 3.6 (5.7)
Overall MMRM results | LS mean (SE) | 15.0 (1.89) | 2.8 (1.52)
Overall MMRM results | LS mean 95% CI | (11.2, 18.9) | (0.0, 5.9)
Overall MMRM results | Difference from placebo:
Overall MMRM results | LS mean difference (SE) | 12.3 (2.49) | -
Overall MMRM results | LS mean difference 95% CI | (7.2, 17.4) | -
Overall MMRM results | P-value | <0.0001 | -

1 - The results are based on an MMRM analysis with time above threshold as a dependent variable; treatment, visit (Weeks 13, 26, 39 and 52), treatment*visit, Ig use (randomization strata), and baseline time above threshold as covariates; and patient as the repeated random effect.

Figure 2: TATANCOver Time (Hours) (LS Mean ± 95% CI) by Treatment Group (Study 1)

Abbreviations: ANC = absolute neutrophil count; CI = confidence interval; LS = least squares; TAT = total time (hours) above threshold (500 cells/µL) in 24 hours.
^1At Week 52, 3 of 17 placebo patients were given XOLREMDI in advance of their TAT measurements as they entered the open-label period of the study; one XOLREMDI patient did not take XOLREMDI. All data were included in the ITT analysis.

For ALC, the mean time (hours) above ALC threshold (TATALC) of 1,000 cells/µL over a 24-hour period was assessed 4 times throughout the study (every 3 months for 12 months). The results over the 52-week period showed that TATALCwas statistically significantly greater in patients treated with XOLREMDI (LS mean [SE] 15.8 [1.39] hours) compared with placebo (4.6 [1.15] hours) (p value <0.0001).

The efficacy of XOLREMDI was further assessed in a composite endpoint consisting of total infection score and total wart change score using a Win-Ratio method (Table 4). The Win-Ratio of 2.76 is the number of pairs of XOLREMDI-treated patient "wins" divided by the number of pairs of placebo patient "wins."

Table 4: Win-Ratio Analysis [The method compared each XOLREMDI-treated patient to each placebo-treated patient in a pair-wise manner that proceeded in a hierarchical fashion using total infection score, followed by total wart change score if patients could not be differentiated based on total infection score. The total infection score was calculated by summing up the number of infection events weighted by severity and divided by the total exposure time (in years). Total wart change score was calculated by summing up the regional wart change scores from all 3 target regions (lesions).] for the Composite Clinical Efficacy Endpoint Based on Total Infection Score and Total Wart Change Score
Category | n [n is number of wins.] | Win-Ratio (95%CI)
XOLREMDI wins on total infection score | 174 | 2.76 (1.60, 4.76)
Placebo wins on total infection score | 63 | 2.76 (1.60, 4.76)
XOLREMDI wins on total wart change score | 0 | 2.76 (1.60, 4.76)
Placebo wins on total wart change score | 0 | 2.76 (1.60, 4.76)
None of the above (tie) | 1 | 2.76 (1.60, 4.76)

Analyses of the individual components of this composite endpoint showed an approximately 40% reduction of total infection score, weighted by infection severity, in XOLREMDI-treated patients compared with placebo-treated patients. The annualized infection rate was reduced approximately 60% in XOLREMDI-treated patients [LS mean (SE) 1.7(0.5)] compared with placebo-treated patients [LS mean (SE) 4.2(0.7)]. There was no difference in total wart change scores between the XOLREMDI and placebo treatment arms over the 52-week period.

16 HOW SUPPLIED/STORAGE AND HANDLING

XOLREMDI is supplied as an opaque white, hard gelatin capsule with a light blue cap, containing 100 mg of the active ingredient mavorixafor. The white capsule body is axially imprinted with "100 mg" in black ink, and the light blue capsule cap is axially imprinted with "MX4" in black ink.

XOLREMDI is supplied in child-resistant bottles as follows:

- 60 count– NDC 83296-100-60
- 90 count - NDC 83296-100-90
- 120 count– NDC 83296-100-12

STORAGE AND HANDLING

Store XOLREMDI refrigerated at 2°C to 8°C (36°F to 46°F). Keep bottle tightly closed. Store in and dispense from original container to protect from moisture.

17 PATIENT COUNSELING INFORMATION

Administration

Advise patients to take XOLREMDI on an empty stomach after an overnight fast, 30 minutes before food. Advise patients to swallow the capsules whole and not to open, break, or chew capsules [see Dosage and Administration (2.1)and Clinical Pharmacology (12.3)] .

Embryo-Fetal Toxicity

XOLREMDI is expected to cause fetal harm. Advise females of reproductive potential to use an effective form of contraception during treatment with XOLREMDI and for 3 weeks after the final dose. Advise females to inform their healthcare provider of a known or suspected pregnancy [see Warnings and Precautions (5.1)and Use In Specific Populations (8.1)] .

Lactation

Advise females that breastfeeding is not recommended during treatment with XOLREMDI and for 3 weeks after the final dose [see Use in Specific Populations (8.2)] .

Drug Interactions

Advise patients to avoid taking dietary supplements that include goldenseal, as it is a strong CYP3A4 inhibitor and may increase risk of adverse reactions to XOLREMDI.

Advise patients to avoid taking dietary supplements that include St. John's Wort, as it is an inducer of CYP3A4 and may reduce the efficacy of XOLREMDI [see Drug Interactions (7.2)] .

Food Interactions

Advise patients to avoid eating or drinking products with grapefruit, as grapefruit is a strong CYP3A4 inhibitor and may increase the risk of adverse reactions to XOLREMDI [see Drug Interactions (7.1)] .

PRINCIPAL DISPLAY PANEL - 100 mg Capsule Bottle Label

NDC 83296-100-60

XOLREMDI™
(mavorixafor) capsules

100 mg

Swallow the capsules whole.
Do not open, break, or chew capsules.

Rx only

60 capsules